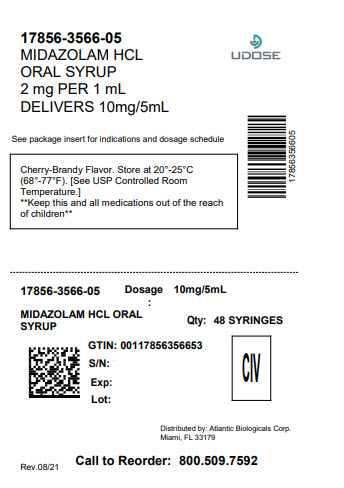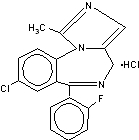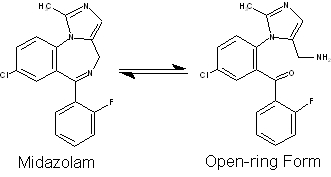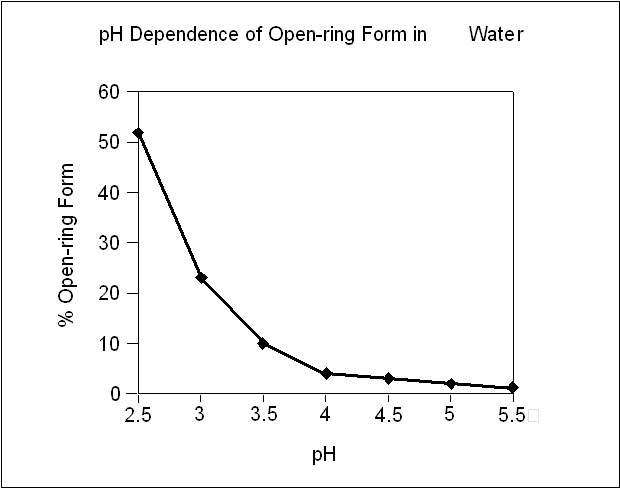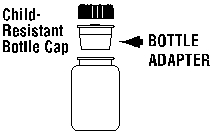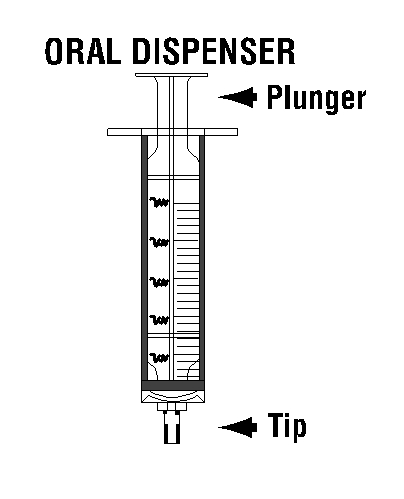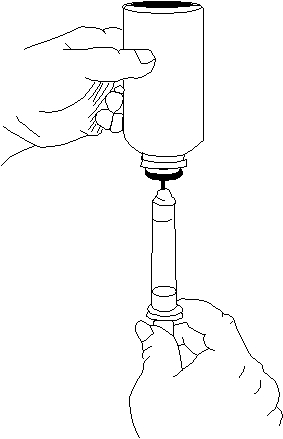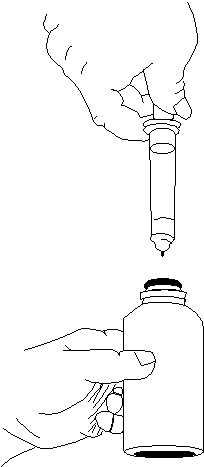 DRUG LABEL: Midazolam Hydrochloride
NDC: 17856-3566 | Form: SYRUP
Manufacturer: ATLANTIC BIOLOGICALS CORP.
Category: prescription | Type: HUMAN PRESCRIPTION DRUG LABEL
Date: 20240521
DEA Schedule: CIV

ACTIVE INGREDIENTS: MIDAZOLAM HYDROCHLORIDE 2 mg/1 mL
INACTIVE INGREDIENTS: ANHYDROUS CITRIC ACID; D&C RED NO. 33; EDETATE DISODIUM; GLYCERIN; HYDROCHLORIC ACID; SODIUM BENZOATE; SODIUM CITRATE; SACCHARIN SODIUM; SORBITOL; WATER

MIDAZOLAM HYDROCHLORIDE SYRUP

BOX WARNING

BOXED WARNING

Midazolam HCl syrup has been associated with respiratory depression and respiratory arrest, especially when used for sedation in noncritical care settings. Midazolam HCl syrup has been associated with reports of respiratory depression, airway obstruction, desaturation, hypoxia, and apnea, most often when used concomitantly with other central nervous system depressants (eg, opioids). Midazolam HCl syrup should be used only in hospital or ambulatory care settings, including physicians’ and dentists’ offices, THAT CAN PROVIDE FOR CONTINUOUS MONITORING OF RESPIRATORY AND CARDIAC FUNCTION. IMMEDIATE AVAILABILITY OF RESUSCITATIVE DRUGS AND AGE- AND SIZE-APPROPRIATE EQUIPMENT FOR VENTILATION AND INTUBATION, AND PERSONNEL TRAINED IN THEIR USE AND SKILLED IN AIRWAY MANAGEMENT SHOULD BE ASSURED (see). For deeply sedated patients, a dedicated individual, other than the practitioner performing the procedure, should monitor the patient throughout the procedure. WARNINGS

DESCRIPTION

Midazolam is a benzodiazepine available as midazolam HCl syrup for oral administration. Midazolam, a white to light yellow crystalline compound, is insoluble in water, but can be solubilized in aqueous solutions by formation of the hydrochloride salt under acidic conditions. Chemically, midazolam HCl is 8-chloro-6-(2-fluorophenyl)-1-methyl-4 -imidazo[1,5-a][1,4]benzodiazepine hydrochloride. in situ H

Midazolam hydrochloride has the molecular formula C H ClFN·HCl, a calculated molecular weight of 362.25 and the following structural formula:1813

Each mL of the syrup contains midazolam hydrochloride equivalent to 2 mg midazolam compounded with artificial bitterness modifier, cherry-brandy flavor, citric acid anhydrous, D&C Red #33, edetate disodium, glycerin, sodium benzoate, sodium citrate, sodium saccharin, sorbitol, and water; the pH is adjusted to 2.8 to 3.6 with hydrochloric acid.

Under the acidic conditions required to solubilize midazolam in the syrup, midazolam is present as an equilibrium mixture (shown below) of the closed ring form shown above and an open-ring structure formed by the acid-catalyzed ring opening of the 4,5-double bond of the diazepine ring. The amount of open-ring form is dependent upon the pH of the solution. At the specified pH of the syrup, the solution may contain up to about 40% of the open-ring compound. At the physiologic conditions under which the product is absorbed (pH of 5 to 8) into the systemic circulation, any open-ring form present reverts to the physiologically active, lipophilic, closed-ring form (midazolam) and is absorbed as such.

The following chart below plots the percentage of midazolam present as the open-ring form as a function of pH in aqueous solutions. As indicated in the graph, the amount of open-ring compound present in solution is sensitive to changes in pH over the pH range specified for the product: 2.8 to 3.6. Above pH 5, at least 99% of the mixture is present in the closed-ring form.

CLINICAL PHARMACOLOGY

Midazolam is a short-acting benzodiazepine central nervous system (CNS) depressant.

Pharmacodynamics

Pharmacodynamic properties of midazolam and its metabolites, which are similar to those of other benzodiazepines, include sedative, anxiolytic, amnesic and hypnotic activities. Benzodiazepine pharmacologic effects appear to result from reversible interactions with the γ-amino butyric acid (GABA) benzodiazepine receptor in the CNS, the major inhibitory neurotransmitter in the central nervous system. The action of midazolam is readily reversed by the benzodiazepine receptor antagonist, flumazenil.

Data from published reports of studies in pediatric patients clearly demonstrate that oral midazolam provides safe and effective sedation and anxiolysis prior to surgical procedures that require anesthesia as well as before other procedures that require sedation but may not require anesthesia. The most commonly reported effective doses range from 0.25 to 1.0 mg/kg in children (6 months to <16 years). The single most commonly reported effective dose is 0.5 mg/kg. Time to onset of effect is most frequently reported as 10 to 20 minutes.

The effects of midazolam on the CNS are dependent on the dose administered, the route of administration, and the presence or absence of other medications.

Following premedication with oral midazolam, time to recovery has been assessed in pediatric patients using various measures, such as time to eye opening, time to extubation, time in the recovery room, and time to discharge from the hospital. Most placebo-controlled trials (8 total) have shown little effect of oral midazolam on recovery time from general anesthesia; however, a number of other placebo-controlled studies (5 total) have demonstrated some prolongation in recovery time following premedication with oral midazolam. Prolonged recovery may be related to duration of the surgical procedure and/or use of other medications with central nervous system depressant properties.

Partial or complete impairment of recall following oral midazolam has been demonstrated in several studies. Amnesia for the surgical experience was greater after oral midazolam when used as a premedicant than after placebo and was generally considered a benefit. In one study, 69% of midazolam patients did not remember mask application versus 6% of placebo patients.

Episodes of oxygen desaturation, respiratory depression, apnea, and airway obstruction have been reported in <1% of pediatric patients following premedication (eg, sedation prior to induction of anesthesia) with midazolam HCl syrup; the potential for such adverse events are markedly increased when oral midazolam is combined with other central nervous system depressing agents and in patients with abnormal airway anatomy, patients with cyanotic congenital heart disease, or patients with sepsis or severe pulmonary disease (see). WARNINGS

Concomitant use of barbiturates or other central nervous system depressants may increase the risk of hypoventilation, airway obstruction, desaturation or apnea, and may contribute to profound and/or prolonged drug effect. In one study of pediatric patients undergoing elective repair of congenital cardiac defects, premedication regimens (oral dose of 0.75 mg/kg midazolam or IM morphine plus scopolamine) increased transcutaneous carbon dioxide (PtcCO), decreased SpO (as measured by pulse oximetry), and decreased respiratory rates preferentially in patients with pulmonary hypertension. This suggests that hypercarbia or hypoxia following premedication might pose a risk to children with congenital heart disease and pulmonary hypertension. In a study of an adult population 65 years and older, the preinduction administration of oral midazolam 7.5 mg resulted in a 60% incidence of hypoxemia (paO <90% for over 30 seconds) at some time during the operative procedure versus 15% for the nonpremedicated group.222

Pharmacokinetics

Absorption

Midazolam is rapidly absorbed after oral administration and is subject to substantial intestinal and hepatic first-pass metabolism. The pharmacokinetics of midazolam and its major metabolite, α-hydroxymidazolam, and the absolute bioavailability of midazolam HCl syrup were studied in pediatric patients of different ages (6 months to <16 years old) over a 0.25 to 1.0 mg/kg dose range. Pharmacokinetic parameters from this study are presented in Table 1. The mean T values across dose groups (0.25, 0.5, and 1.0 mg/kg) range from 0.17 to 2.65 hours. Midazolam exhibits linear pharmacokinetics between oral doses of 0.25 to 1.0 mg/kg (up to a maximum dose of 40 mg) across the age groups ranging from 6 months to <16 years. Linearity was also demonstrated across the doses within the age group of 2 years to <12 years having 18 patients at each of the three doses. The absolute bioavailability of the midazolam HCl syrup in pediatric patients is about 36%, which is not affected by pediatric age or weight. The AUC ratio of α-hydroxymidazolam to midazolam for the oral dose in pediatric patients is higher than for an IV dose (0.38 to 0.75 versus 0.21 to 0.39 across the age group of 6 months to <16 years), and the AUC ratio of a-hydroxymidazolam to midazolam for the oral dose is higher in pediatric patients than in adults (0.38 to 0.75 versus 0.40 to 0.56).max0-∞0-∞

Food effect has not been tested using midazolam HCl syrup. When a 15 mg oral tablet of midazolam was administered with food to adults, the absorption and disposition of midazolam was not affected. Feeding is generally contraindicated prior to sedation of pediatric patients for procedures.

Table 1

Pharmacokinetics of Midazolam Following Single Dose Administration of Midazolam HCl Syrup
Number of subjects/age group | Dose (mg/kg) | T (h)max | C (ng/mL)max | t (h)1/2 | AUC (ng•h/mL)0-∞
6 months to <2 years old
1 | 0.25 | 0.17 | 28.0 | 5.82 | 67.6
1 | 0.50 | 0.35 | 66.0 | 2.22 | 152
1 | 1.00 | 0.17 | 61.2 | 2.97 | 224
2 to <12 years old
18 | 0.25 | 0.72 ± 0.44 | 63.0 ± 30.0 | 3.16 ± 1.50 | 138 ± 89.5
18 | 0.50 | 0.95 ± 0.53 | 126 ± 75.8 | 2.71 ± 1.09 | 306 ± 196
18 | 1.00 | 0.88 ± 0.99 | 201 ± 101 | 2.37 ± 0.96 | 743 ± 642
12 to <16 years old
4 | 0.25 | 2.09 ± 1.35 | 29.1 ± 8.2 | 6.83 ± 3.84 | 155 ± 84.6
4 | 0.50 | 2.65 ±1.58 | 118 ± 81.2 | 4.35 ± 3.31 | 821 ± 568
2 | 1.00 | 0.55 ± 0.28 | 191 ± 47.4 | 2.51 ± 0.18 | 566 ±15.7

Distribution

The extent of plasma protein binding of midazolam is moderately high and concentration independent. In adults and pediatric patients older than 1 year, midazolam is approximately 97% bound to plasma protein, principally albumin. In healthy volunteers, a-hydroxymidazolam is bound to the extent of 89%. In pediatric patients (6 months to <16 years) receiving 0.15 mg/kg IV midazolam, the mean steady-state volume of distribution ranged from 1.24 to 2.02 L/kg.

Metabolism

Midazolam is primarily metabolized in the liver and gut by human cytochrome P450 IIIA4 (CYP3A4) to its pharmacologic active metabolite, α-hydroxymidazolam, followed by glucuronidation of the α-hydroxyl metabolite which is present in unconjugated and conjugated forms in human plasma. The α-hydroxymidazolam glucuronide is then excreted in urine. In a study in which adult volunteers were administered intravenous midazolam (0.1 mg/kg) and a-hydroxymidazolam (0.15 mg/kg), the pharmacodynamic parameter values of the maximum effect (E) and concentration eliciting half-maximal effect (EC) were similar for both compounds. The effects studied were reaction time and errors in tracing tests. The results indicate that α-hydroxymidazolam is equipotent and equally effective as unchanged midazolam on a total plasma concentration basis. After oral or intravenous administration, 63% to 80% of midazolam is recovered in urine as α-hydroxymidazolam glucuronide. No significant amount of parent drug or metabolites is extractable from urine before beta-glucuronidase and sulfatase deconjugation, indicating that the urinary metabolites are excreted mainly as conjugates.max50

Midazolam is also metabolized to two other minor metabolites: 4-hydroxy metabolite (about 3% of the dose) and 1,4-dihydroxy metabolite (about 1% of the dose) are excreted in small amounts in the urine as conjugates.

Elimination

The mean elimination half-life of midazolam ranged from 2.2 to 6.8 hours following single oral doses of 0.25, 0.5, and 1.0 mg/kg of midazolam HCl syrup. Similar results (ranged from 2.9 to 4.5 hours) for the mean elimination half-life were observed following IV administration of 0.15 mg/kg of midazolam to pediatric patients (6 months to <16 years old). In the same group of patients receiving the 0.15 mg/kg IV dose, the mean total clearance ranged from 9.3 to 11.0 mL/min/kg.

Pharmacokinetic-Pharmacodynamic Relationships

The relationship between plasma concentration and sedation and anxiolysis scores of midazolam syrup (single oral doses of 0.25, 0.5, or 1.0 mg/kg) was investigated in three age groups of pediatric patients (6 months to <2 years, 2 to <12 years, and 12 to <16 years old). In this study, the patient’s sedation scores were recorded at baseline and at 10-minute intervals up to 30 minutes after oral dosing until satisfactory sedation (“drowsy” or “asleep but responsive to mild shaking” or “asleep and not responsive to mild shaking”) was achieved. Anxiolysis scores were measured at the time when the patient was separated from his/her parents and at mask induction. The results of the analyses showed that the mean midazolam plasma concentration as well as the mean of midazolam plus α-hydroxymidazolam for those patients with a sedation score of 4 (asleep but responsive to mild shaking) is significantly different than the mean concentrations for those patients with a sedation score of 3 (drowsy), which is significantly different than the mean concentrations for patients with a sedation score of 2 (awake/calm). The statistical analysis indicates that the greater the midazolam, or midazolam plus a-hydroxymidazolam concentration, the greater the maximum sedation score for pediatric patients. No such trend was observed between anxiolysis scores and the mean midazolam concentration or mean of midazolam plus a-hydroxymidazolam concentration, however, anxiolysis is a more variable surrogate measurement of clinical response.

Special Populations

Renal Impairment

Although the pharmacokinetics of intravenous midazolam in adult patients with chronic renal failure differed from those of subjects with normal renal function, there were no alterations in the distribution, elimination, or clearance of unbound drug in the renal failure patients. However, the effects of renal impairment on the active metabolite α-hydroxymidazolam are unknown.

Hepatic Dysfunction

Chronic hepatic disease alters the pharmacokinetics of midazolam. Following oral administration of 15 mg of midazolam, C and bioavailability values were 43% and 100% higher, respectively, in adult patients with hepatic cirrhosis than adult subjects with normal liver function. In the same patients with hepatic cirrhosis, following IV administration of 7.5 mg of midazolam, the clearance of midazolam was reduced by about 40% and the elimination half-life was increased by about 90% compared with subjects with normal liver function. Midazolam should be titrated for the desired effect in patients with chronic hepatic disease.max

Congestive Heart Failure

Following oral administration of 7.5 mg of midazolam, elimination half-life values were 43% higher in adult patients with congestive heart failure than in control subjects.

Neonates

Midazolam HCl syrup has not been studied in pediatric patients less than 6 months of age.

Drug-Drug Interactions

See : . PRECAUTIONSDrug Interactions

INHIBITORS OF CYP3A4 ISOZYMES

Table 2 summarizes the changes in the C and AUC of midazolam when drugs known to inhibit CYP3A4 were concurrently administered with oral midazolam in adult subjects.max

Table 2

Interacting Drug | Adult Doses Studied | % Increase in C of Oral Midazolam max | % Increase in AUC of Oral Midazolam
Cimetidine | 800-1200 mg up to qid in divided doses | 6-138 | 10-102
Diltiazem | 60 mg tid | 105 | 275
Erythromycin | 500 mg tid | 170-171 | 281-341
Fluconazole | 200 mg qd | 150 | 250
Grapefruit Juice | 200 mL | 56 | 52
Itraconazole | 100-200 mg qd | 80-240 | 240-980
Ketoconazole | 400 mg qd | 309 | 1490
Ranitidine | 150 mg bid or tid; 300 mg qd | 15-67 | 9-66
Roxithromycin | 300 mg qd | 37 | 47
Saquinavir | 1200 mg tid | 235 | 514
Verapamil | 80 mg tid | 97 | 192

Other drugs known to inhibit the effects of CYP3A4, such as protease inhibitors, would be expected to have similar effects on these midazolam pharmacokinetic parameters.

INDUCERS OF CYP3A4 ISOZYMES

Table 3 summarizes the changes in the C and AUC of midazolam when drugs known to induce CYP3A4 were concurrently administered with oral midazolam in adult subjects. The clinical significance of these changes is unclear.max

Table 3

Interacting Drug | Adult Doses Studied | % Decrease in C of Oral Midazolam max | % Decrease in AUC of Oral Midazolam
Carbamazepine | Therapeutic Doses | 93 | 94
Phenytoin | Therapeutic Doses | 93 | 94
Rifampin | 600 mg/day | 94 | 96

Although not tested, phenobarbital, rifabutin and other drugs known to induce the effects of CYP3A4 would be expected to have similar effects on these midazolam pharmacokinetic parameters.

Drugs that did not affect midazolam pharmacokinetics are presented in Table 4.

Table 4

Interacting Drug | Adult Doses Studied
Azithromycin | 500 mg/day
Nitrendipine | 20 mg
Terbinafine | 200 mg/day

Clinical Trials

Dose Ranging, Safety and Efficacy Study With Midazolam HCl Syrup in Pediatric Patients

The effectiveness of midazolam HCl syrup as a premedicant to sedate and calm pediatric patients prior to induction of general anesthesia was compared among three different doses in a randomized, double-blind, parallel-group study. Patients of ASA physical status I, II or III were stratified to 1 of 3 age groups (6 months to <2 years, 2 to <6 years, and 6 to <16 years), and within each age group randomized to 1 of 3 dosing groups (0.25, 0.5, and 1.0 mg/kg up to a maximum dose of 20 mg). Greater than 90% of treated patients achieved satisfactory sedation and anxiolysis at at least one timepoint within 30 minutes posttreatment. Similarly high proportions of patients exhibited satisfactory ease of separation from parent or guardian and were cooperative at the time of mask induction with nitrous oxide and halothane administration. Onset time of satisfactory sedation or anxiolysis occurred within 10 minutes after treatment for >70% of patients who started with an unsatisfactory baseline rating. Whereas pairwise comparisons (0.25 mg/kg versus 0.5 mg/kg groups, and 0.5 mg/kg versus 1.0 mg/kg groups) on satisfactory sedation did not yield significant p-values (p=0.08 in both cases), comparative analysis of the clinical response between the high and low doses demonstrated that a higher proportion of patients in the 1.0 mg/kg dose group exhibited satisfactory sedation and anxiolysis as compared to the 0.25 mg/kg group (p<0.05).

INDICATIONS AND USAGE

Midazolam HCl Syrup is indicated for use in pediatric patients for sedation, anxiolysis and amnesia prior to diagnostic, therapeutic or endoscopic procedures or before induction of anesthesia.

Midazolam HCl syrup is intended for use in monitored settings only and not for chronic or home use (see). WARNINGSMIDAZOLAM HCL SYRUP MUST BE USED AS SPECIFIED IN THE LABEL.

Midazolam is associated with a high incidence of partial or complete impairment of recall for the next several hours (see). CLINICAL PHARMACOLOGY

CONTRAINDICATIONS

Midazolam is contraindicated in patients with a known hypersensitivity to the drug or allergies to cherries or formulation excipients. Benzodiazepines are contraindicated in patients with acute narrow-angle glaucoma. Benzodiazepines may be used in patients with open-angle glaucoma only if they are receiving appropriate therapy. Measurements of intraocular pressure in patients without eye disease show a moderate lowering following induction of general anesthesia with injectable midazolam; patients with glaucoma have not been studied.

WARNINGS

(). (). Serious respiratory adverse events have occurred after administration of oral midazolam, most often when midazolam was used in combination with other central nervous system depressants. These adverse events have included respiratory depression, airway obstruction, oxygen desaturation, apnea, and rarely, respiratory and/or cardiac arrestsee BOX WARNINGWhen oral midazolam is administered as the sole agent at recommended doses respiratory depression, airway obstruction, oxygen desaturation, and apnea occur infrequentlysee DOSAGE AND ADMINISTRATION

Prior to the administration of midazolam in any dose, the immediate availability of oxygen, resuscitative drugs, age- and size-appropriate equipment for bag/valve/mask ventilation and intubation, and skilled personnel for the maintenance of a patent airway and support of ventilation should be ensured. Midazolam HCl syrup must never be used without individualization of dosage, particularly when used with other medications capable of producing central nervous system depression.

Midazolam HCl syrup should be used only in hospital or ambulatory care settings, including physicians’ and dentists’ offices, that are equipped to provide continuous monitoring of respiratory and cardiac function. Midazolam HCl syrup must only be administered to patients if they will be monitored by direct visual observation by a health care professional. If midazolam HCl syrup will be administered in combination with other anesthetic drugs or drugs which depress the central nervous system, patients must be monitored by persons specifically trained in the use of these drugs and, in particular, in the management of respiratory effects of these drugs, including respiratory and cardiac resuscitation of patients in the age group being treated.

For deeply sedated patients, a dedicated individual whose sole responsibility is to observe the patient, other than the practitioner performing the procedure, should monitor the patient throughout the procedure.

. The immediate availability of specific reversal agents (flumazenil) is highly recommended. Vital signs should continue to be monitored during the recovery period. Because midazolam can depress respiration (see), especially when used concomitantly with opioid agonists and other sedatives (see), it should be used for sedation/anxiolysis/amnesia only in the presence of personnel skilled in early detection of hypoventilation, maintaining a patent airway, and supporting ventilation. Patients should be continuously monitored for early signs of hypoventilation, airway obstruction, or apnea with means for detection readily available (eg, pulse oximetry). Hypoventilation, airway obstruction, and apnea can lead to hypoxia and/or cardiac arrest unless effective countermeasures are taken immediately CLINICAL PHARMACOLOGYDOSAGE AND ADMINISTRATION

Episodes of oxygen desaturation, respiratory depression, apnea, and airway obstruction have been occasionally reported following premedication (sedation prior to induction of anesthesia) with oral midazolam; such events are markedly increased when oral midazolam is combined with other central nervous system depressing agents and in patients with abnormal airway anatomy, patients with cyanotic congenital heart disease, or patients with sepsis or severe pulmonary disease.

Reactions such as agitation, involuntary movements (including tonic/clonic movements and muscle tremor), hyperactivity and combativeness have been reported in both adult and pediatric patients. Consideration should be given to the possibility of paradoxical reaction. Should such reactions occur, the response to each dose of midazolam and all other drugs, including local anesthetics, should be evaluated before proceeding. Reversal of such responses with flumazenil has been reported in pediatric and adult patients.

Concomitant use of barbiturates, alcohol or other central nervous system depressants may increase the risk of hypoventilation, airway obstruction, desaturation, or apnea and may contribute to profound and/or prolonged drug effect. Narcotic premedication also depresses the ventilatory response to carbon dioxide stimulation.

Coadministration of oral midazolam in patients who are taking ketoconazole, intraconazole, and saquinavir has been shown to result in large increases in C and AUC of midazolam due to a decrease in plasma clearance of midazolam (see : and). Due to the potential for intense and prolonged sedation and respiratory depression, midazolam syrup should only be coadministered with these medications if absolutely necessary and with appropriate equipment and personnel available to respond to respiratory insufficiency.max Pharmacokinetics Drug-Drug Interactions PRECAUTIONS

Higher risk pediatric surgical patients may require lower doses, whether or not concomitant sedating medications have been administered. Pediatric patients with cardiac or respiratory compromise may be unusually sensitive to the respiratory depressant effect of midazolam. Pediatric patients undergoing procedures involving the upper airway such as upper endoscopy or dental care, are particularly vulnerable to episodes of desaturation and hypoventilation due to partial airway obstruction. Patients with chronic renal failure and patients with congestive heart failure eliminate midazolam more slowly (see). CLINICAL PHARMACOLOGY

The decision as to when patients who have received midazolam HCl syrup, particularly on an outpatient basis, may again engage in activities requiring complete mental alertness, operate hazardous machinery or drive a motor vehicle must be individualized. Gross tests of recovery from the effects of midazolam HCl syrup (see) cannot be relied upon to predict reaction time under stress. It is recommended that no patient operate hazardous machinery or a motor vehicle until the effects of the drug, such as drowsiness, have subsided or until one full day after anesthesia and surgery, whichever is longer. Particular care should be taken to assure safe ambulation. CLINICAL PHARMACOLOGY

Usage in Pregnancy

Although midazolam HCl syrup has not been studied in pregnant patients, an increased risk of congenital malformations associated with the use of benzodiazepine drugs (diazepam and chlordiazepoxide) have been suggested in several studies. If this drug is used during pregnancy, the patient should be apprised of the potential hazard to the fetus.

Usage in Preterm Infants and Neonates

Midazolam HCl syrup has not been studied in patients less than 6 months of age.

PRECAUTIONS

Use With Other CNS Depressants

The efficacy and safety of midazolam in clinical use are functions of the dose administered, the clinical status of the individual patient, and the use of concomitant medications capable of depressing the CNS. Anticipated effects may range from mild sedation to deep levels of sedation with a potential loss of protective reflexes, particularly when coadministered with anesthetic agents or other CNS depressants. Care must be taken to individualize the dose of midazolam based on the patient’s age, underlying medical/surgical conditions, concomitant medications, and to have the personnel, age- and size-appropriate equipment and facilities available for monitoring and intervention. Practitioners administering midazolam must have the skills necessary to manage reasonably foreseeable adverse effects, particularly skills in airway management.

Use With Inhibitors of CYP3A4 Isozymes

Oral midazolam should be used with caution in patients treated with drugs known to inhibit CYP3A4 because inhibition of metabolism may lead to more intense and prolonged sedation (see : and). Patients being treated with medications known to inhibit CYP3A4 isozymes should be treated with lower than recommended doses of midazolam HCl syrup and the clinician should expect a more intense and prolonged effect. Pharmacokinetics Drug-Drug Interactions WARNINGS

Information for Patients

To assure safe and effective use of midazolam HCl syrup, the following information and instructions should be communicated to the patient when appropriate:

1. Inform your physician about any alcohol consumption and medicine you are now taking, especially blood pressure medication, antibiotics, and protease inhibitors, including drugs you buy without a prescription. Alcohol has an increased effect when consumed with benzodiazepines; therefore, caution should be exercised regarding simultaneous ingestion of alcohol during benzodiazepine treatment.
2. Inform your physician if you are pregnant or are planning to become pregnant.
3. Inform your physician if you are nursing.
4. Patients should be informed of the pharmacological effects of midazolam HCl syrup, such as sedation and amnesia, which in some patients may be profound. The decision as to when patients who have received midazolam HCl syrup, particularly on an outpatient basis, may again engage in activities requiring complete mental alertness, operate hazardous machinery or drive a motor vehicle must be individualized.
5. Midazolam HCl syrup should not be taken in conjunction with grapefruit juice.
6. For pediatric patients, particular care should be taken to assure safe ambulation.

Drug Interactions

Inhibitors of CYP3A4 Isozymes

Caution is advised when midazolam is administered concomitantly with drugs that are known to inhibit the cytochrome P450 3A4 enzyme system (ie, some drugs in the drug classes of azole antimycotics, protease inhibitors, calcium channel antagonists, and macrolide antibiotics). Drugs such as diltiazem, erythromycin, fluconazole, itraconazole, ketoconazole, saquinavir, and verapamil were shown to significantly increase the C and AUC of orally administered midazolam. These drug interactions may result in increased and prolonged sedation due to a decrease in plasma clearance of midazolam. Although not studied, the potent cytochrome P450 3A4 inhibitors ritanovir and nelfinavir may cause intense and prolonged sedation and respiratory depression due to a decrease in plasma clearance of midazolam. Caution is advised when midazolam HCl syrup is used concomitantly with these drugs. Dose adjustments should be considered and possible prolongation and intensity of effect should be anticipated (see :).max Pharmacokinetics Drug-Drug Interactions

Inducers of CYP3A4 Isozymes

Cytochrome P450 inducers, such as rifampin, carbamazepine, and phenytoin, induce metabolism and cause a markedly decreased C and AUC of oral midazolam in adult studies. Although clinical studies have not been performed, phenobarbital is expected to have the same effect. Caution is advised when administering midazolam HCl syrup to patients receiving these medications and if necessary dose adjustments should be considered.max

CNS Depressants

One case was reported of inadequate sedation with chloral hydrate and later with oral midazolam due to a possible interaction with methylphenidate administered chronically in a 2-year-old boy with a history of Williams syndrome. The difficulty in achieving adequate sedation may have been the result of decreased absorption of the sedatives due to both the gastrointestinal effects and stimulant effects of methylphenidate.

The sedative effect of midazolam HCl syrup is accentuated by any concomitantly administered medication which depresses the central nervous system, particularly narcotics (eg, morphine, meperidine and fentanyl), propofol, ketamine, nitrous oxide, secobarbital and droperidol. Consequently, the dose of midazolam HCl syrup should be adjusted according to the type and amount of concomitant medications administered and the desired clinical response (see). DOSAGE AND ADMINISTRATION

No significant adverse interactions with common premedications (such as atropine, scopolamine, glycopyrrolate, diazepam, hydroxyzine, and other muscle relaxants) or local anesthetics have been observed.

Drug/Laboratory Test Interactions

Midazolam has not been shown to interfere with results obtained in clinical laboratory tests.

Carcinogenesis, Mutagenesis, Impairment of Fertility

Carcinogenesis

Midazolam maleate was administered with diet in mice and rats for 2 years at dosages of 1, 9, and 80 mg/kg/day. In female mice in the highest dose (10 times the highest oral dose of 1.0 mg/kg for a pediatric patient, on a mg/m basis) group there was a marked increase in the incidence of hepatic tumors. In high-dose (19 times the pediatric dose) male rats there was a small but statistically significant increase in benign thyroid follicular cell tumors. Dosages of 9 mg/kg/day of midazolam maleate (1 to 2 times the pediatric dose) did not increase the incidence of tumors in mice or rats. The pathogenesis of induction of these tumors is not known. These tumors were found after chronic administration, whereas human use will ordinarily be single or intermittent doses.^2

Mutagenesis

Midazolam did not have mutagenic activity in Salmonella typhimurium (5 bacterial strains), Chinese hamster lung cells (V79), human lymphocytes or in the micronucleus test in mice.

Impairment of Fertility

A reproduction study in male and female rats did not show any impairment of fertility at dosages up to 16 mg/kg/day PO (3 times the human dose of 1.0 mg/kg, on a mg/m basis).^2

Pregnancy

Teratogenic Effects

Pregnancy Category D (see). WARNINGS

Embryo-fetal development studies, performed with midazolam maleate in mice (at up to 120 mg/kg/day PO, 10 times the human dose of 1.0 mg/kg on a mg/m basis), rats (at up to 4 mg/kg/day IV, 8 times the human IV dose of 5 mg) and rabbits (at up to 100 mg/kg/day PO, 32 times the human oral dose of 1.0 mg/kg on a mg/m basis), did not show evidence of teratogenicity.^2^2

Nonteratogenic Effects

Studies in rats showed no adverse effects on reproductive parameters during gestation and lactation. Dosages tested (4 mg/kg IV and 50 mg/kg PO) were approximately 8 times each the human doses on a mg/m basis.^2

Labor and Delivery

In humans, measurable levels of midazolam were found in maternal venous serum, umbilical venous and arterial serum and amniotic fluid, indicating placental transfer of the drug.

The use of midazolam HCl syrup in obstetrics has not been evaluated in clinical studies. Because midazolam is transferred transplacentally and because other benzodiazepines given in the last weeks of pregnancy have resulted in neonatal CNS depression, midazolam syrup is not recommended for obstetrical use.

Nursing Mothers

Midazolam is excreted in human milk. Caution should be exercised when midazolam syrup is administered to a nursing woman.

Geriatric Use

The safety and efficacy of this product have not been fully studied in geriatric patients. Therefore, there are no available data on a safe dosing regimen. One study in geriatric subjects, using midazolam 7.5 mg as a premedicant prior to general anesthesia, noted a 60% incidence of hypoxemia (pO <90% for over 30 seconds) at sometime during the operative procedure versus 15% for the nonpremedicated group. Until further information is available it is recommended that this product should not be used in geriatric patients.2

Use in Patients With Heart Disease

Following oral administration of 7.5 mg of midazolam to adult patients with congestive heart failure, the half-life of midazolam was 43% higher than in control subjects. One study suggests that hypercarbia or hypoxia following premedication with oral midazolam might pose a risk to children with congenital heart disease and pulmonary hypertension, although there are no known reports of pulmonary hypertensive crisis that had been triggered by premedication. In the study, 22 children were premedicated with oral midazolam (0.75 mg/kg) or IM morphine plus scopolamine prior to elective repair of congenital cardiac defects. Both premedication regimens increased PtcCO and decreased SpO and respiratory rates preferentially in patients with pulmonary hypertension.22

ADVERSE REACTIONS

The distribution of adverse events occurring in patients evaluated in a randomized, double-blind, parallel-group trial are presented in Tables 5 and 6 by body system in order of decreasing frequency: for the premedication period (eg, sedation period prior to induction of anesthesia) alone, see Table 5; for over the entire monitoring period including premedication, anesthesia and recovery, see Table 6.

The distribution of adverse events occurring during the premedication period, before induction of anesthesia, is presented in Table 5. Emesis, which occurred in 31/397 (8%) patients over the entire monitoring period, occurred in 3/397 (0.8%) of patients during the premedication period (from midazolam administration to mask induction). Nausea, which occurred in 14/397 (4%) patients over the entire monitoring period (premedication, anesthesia and recovery), occurred in 2/397 (0.5%) patients during the premedication period.

This distribution of all adverse events occurring in ≥1% of patients over the entire monitoring period are presented in Table 6. For the entire monitoring period (premedication, anesthesia and recovery), adverse events were reported by 82/397 (21%) patients who received midazolam overall. The most frequently reported adverse events were emesis occurring in 31/397 (8%) patients and nausea occurring in 14/397 (4%) patients. Most of these gastrointestinal events occurred after the administration of other anesthetic agents.

For the respiratory system overall, adverse events (hypoxia, laryngospasm, rhonchi, coughing, respiratory depression, airway obstruction, upper-airway congestion, shallow respirations), occurred during the entire monitoring period in 31/397 (8%) patients and increased in frequency as dosage was increased: 7/132 (5%) patients in the 0.25 mg/kg dose group, 9/132 (7%) patients in the 0.5 mg/kg dose group, and 15/133 (11%) patients in the 1.0 mg/kg dose group.

Most of the respiratory adverse events occurred during induction, general anesthesia or recovery. One patient (0.25%) experienced a respiratory system adverse event (laryngospasm) during the premedication period. This adverse event occurred precisely at the time of induction. Although many of the respiratory complications occurred in settings of upper airway procedures or concurrently administered opioids, a number of these events occurred outside of these settings as well. In this study, administration of midazolam HCl syrup was generally accompanied by a slight decrease in both systolic and diastolic blood pressures, as well as a slight increase in heart rate.

Table 5

Adverse Events Offurring During the Premedication Period Before Mask Induction in the Randomized, Double-Blind, Parallel-Group Trial
Body System | Treatment Regimen |  |  | Overall
No. Patients with Adverse Events | 0.25 mg/kg (n=132) No. (%) | 0.50 mg/kg (n=132) No. (%) | 1.0 mg/kg (n=133) No. (%) | (n=397) No. (%)
Gastrointestinal
System Disorders
Emesis | 1 (0.76%) | 1 (0.76%) | 1 (0.75%) | 3 (0.76%)
Nausea |  |  | 2 (1.5%) | 2 (0.50%)
Respiratory
System Disorders
Laryngospasm |  |  | 1 (0.75%) [This adverse event occurred precisely at the time of induction.] | 1 (0.25%)
Sneezing/Rhinorrhea |  |  | 1 (0.75%) | 1 (0.25%)
ALL BODY SYSTEMS | 1 (0.76%) | 1 (0.76%) | 5 (3.8%) | 7 (1.8%)

Table 6

Adverse Events (1%) From the Randomized, Double-blind, Parallel-Group Trial on Entire Monitoring Period (premedication, anesthesia, recovery)
Body System | Treatment Regimen |  |  |  |  |  | Overall
No. Patients with
Adverse Events | 0.25 mg/kg (n=132) |  | 0.50 mg/kg (n=132) |  | 1.0 mg/kg (n=133) |  | (n=397)
 | No. | (%) | No. | (%) | No. | (%) | No. | (%)
Gastrointestinal
System Disorders
Emesis | 11 | (8%) | 5 | (4%) | 15 | (11%) | 31 | (8%)
Nausea | 6 | (5%) | 2 | (2%) | 6 | (5%) | 14 | (4%)
Overall | 16 | (12%) | 8 | (6%) | 16 | (12%) | 40 | (10%)
Respiratory
System Disorders
Hypoxia | 0 |  | 5 | (4%) | 4 | (3%) | 9 | (2%)
Laryngospasm | 0 |  | 1 | (<1%) | 5 | (4%) | 6 | (2%)
Respiratory Depression | 2 | (2%) | 1 | (<1%) | 2 | (2%) | 5 | (1%)
Rhonchi | 2 | (2%) | 1 | (<1%) | 2 | (2%) | 5 | (1%)
Airway Obstruction | 2 | (2%) | 2 | (2%) | 0 |  | 4 | (1%)
Upper Airway Congestion | 2 | (2%) | 0 |  | 2 | (2%) | 4 | (1%)
Overall | 7 | (5%) | 9 | (7%) | 15 | (11%) | 31 | (8%)
Psychiatic Disorders
Agitated | 1 | (<1%) | 2 | (2%) | 3 | (2%) | 6 | (2%)
Overall | 1 | (<1%) | 3 | (2%) | 4 | (3%) | 8 | (2%)
Heart Rate, Rhythm
Disorders
Bradycardia | 1 | (<1%) | 3 | (2%) | 0 |  | 4 | (1%)
Bigeminy | 2 | (2%) | 0 |  | 0 |  | 2 | (<1%)
Overall | 3 | (2%) | 3 | (2%) | 1 | (<1%) | 7 | (2%)
Central & Peripheral
Nervous System Disorders
Prolonged Sedation | 0 |  | 0 |  | 2 | (2%) | 2 | (<1%)
Overall | 2 | (2%) | 0 |  | 3 | (2%) | 5 | (1%)
Skin and Appendages
Disorders
Rash | 2 | (2%) | 0 |  | 0 |  | 2 | (<1%)
Overall | 2 | (2%) | 2 | (2%) | 0 |  | 4 | (1%)
ALL BODY SYSTEMS | 26 | (20%) | 23 | (17%) | 33 | (25%) | 82 | (21%)

There were no deaths during the study and no patient withdrew from the study due to adverse events. Serious adverse events (both respiratory disorders) were experienced postoperatively by two patients: one case of airway obstruction and desaturation (SpO of 33%) in a patient given midazolam HCl syrup 0.25 mg/kg, and one case of upper airway obstruction and respiratory depression following 0.5 mg/kg. Both patients had received intravenous morphine sulfate (1.5 mg total for both patients).2

Other adverse events that have been reported in the literature with the oral administration of midazolam (not necessarily midazolam syrup), are listed below. The incidence rate for these events was generally <1%.

apnea, hypercarbia, desaturation, stridor. Respiratory:

decreased systolic and diastolic blood pressure, increased heart rate. Cardiovascular:

nausea, vomiting, hiccoughs, gagging, salivation, drooling. Gastrointestinal:

Central Nervous System: dysphoria, disinhibition, excitation, aggression, mood swings, hallucinations, adverse behavior, agitation, dizziness, confusion, ataxia, vertigo, dysarthria.

diplopia, strabismus, loss of balance, blurred vision. Special Senses:

DRUG ABUSE AND DEPENDENCE

Midazolam HCl syrup is a benzodiazepine and is a Schedule IV controlled substance that can produce drug dependence of the diazepam-type. Therefore, midazolam HCl syrup may be subject to misuse, abuse and addiction. Benzodiazepines can cause physical dependence. Physical dependence results in withdrawal symptoms in patients who abruptly discontinue the drug. Withdrawal symptoms (ie, convulsions, hallucinations, tremors, abdominal and muscle cramps, vomiting and sweating), similar in characteristics to those noted with barbiturates and alcohol have occurred following abrupt discontinuation of midazolam following chronic administration. Abdominal distention, nausea, vomiting, and tachycardia are prominent symptoms of withdrawal in infants.

The handling of midazolam HCL syrup should be managed to minimize the risk of diversion, including restriction of access and accounting procedures as appropriate to the clinical setting and as required by law.

OVERDOSAGE

The manifestations of midazolam overdosage reported are similar to those observed with other benzodiazepines, including sedation, somnolence, confusion, impaired coordination, diminished reflexes, coma, and deleterious effects on vital signs. No evidence of specific organ toxicity from midazolam overdosage has been reported.

Treatment of Overdosage

Treatment of midazolam overdosage is the same as that followed for overdosage with other benzodiazepines. Respiration, pulse rate and blood pressure should be monitored and general supportive measures should be employed. Attention should be given to the maintenance of a patent airway and support of ventilation, including administration of oxygen. Should hypotension develop, treatment may include intravenous fluid therapy, repositioning, judicious use of vasopressors appropriate to the clinical situation, if indicated, and other appropriate countermeasures. There is no information as to whether peritoneal dialysis, forced diuresis or hemodialysis are of any value in the treatment of midazolam overdosage.

Gastrointestinal decontamination with lavage and/or activated charcoal once the patient’s airway is secure is also recommended.

Flumazenil, a specific benzodiazepine-receptor antagonist, is indicated for the complete or partial reversal of the sedative effects of midazolam and may be used in situations when an overdose with a benzodiazepine is known or suspected. There are anecdotal reports of adverse hemodynamic responses associated with midazolam following administration of flumazenil to pediatric patients. Prior to the administration of flumazenil, necessary measures should be instituted to secure the airway, assure adequate ventilation, and establish adequate intravenous access. Flumazenil is intended as an adjunct to, not as a substitute for, proper management of benzodiazepine overdose. Patients treated with flumazenil should be monitored for resedation, respiratory depression and other residual benzodiazepine effects for an appropriate period after treatment. The prescriber should be aware of a risk of seizure in association with flumazenil treatment, particularly in long-term benzodiazepine users and in cyclic antidepressant overdose. The complete flumazenil package insert, including CONTRAINDICATIONS, WARNINGS and PRECAUTIONS, should be consulted prior to use.

DOSAGE AND ADMINISTRATION

Midazolam HCl syrup is indicated for use as a single dose (0.25 to 1.0 mg/kg with a maximum dose of 20 mg) for preprocedural sedation and anxiolysis in pediatric patients. Midazolam HCl syrup is not intended for chronic administration.

Monitoring

Midazolam HCl syrup should only be used in hospital or ambulatory care settings, including physicians’ and dentists’ offices, that can provide for continuous monitoring of respiratory and cardiac function. Immediate availability of resuscitative drugs and age- and size-appropriate equipment for bag/valve/mask ventilation and intubation, and personnel trained in their use and skilled in airway management should be assured (see). For deeply sedated patients, a dedicated individual whose sole responsibility it is to observe the patient, other than the practitioner performing the procedure, should monitor the patient throughout the procedure. Continuous monitoring of respiratory and cardiac function is required. WARNINGS

Midazolam HCl syrup should only be administered by persons specifically trained in the use of anesthetic drugs and the management of respiratory effects of anesthetic drugs, including respiratory and cardiac resuscitation of patients in the age group being treated. Midazolam HCl syrup must be given only to patients if they will be monitored by direct visual observation by a health care professional.

Patient response to sedative agents, and resultant respiratory status, is variable. Regardless of the intended level of sedation or route of administration, sedation is a continuum; a patient may move easily from light to deep sedation, with potential loss of protective reflexes, particularly when coadministered with anesthetic agents, other CNS depressants, and concomitant medications which may potentially cause a more intense and prolonged sedation (see :). This is especially true in pediatric patients. The health care practitioner who uses this medication in pediatric patients should be aware of and follow accepted professional guidelines for pediatric sedation appropriate to their situation. PRECAUTIONSDrug Interactions

Sedation guidelines recommend a careful presedation history to determine how a patient’s underlying medical conditions or concomitant medications might affect their response to sedation/analgesia as well as a physical examination including a focused examination of the airway for abnormalities. Further recommendations include appropriate presedation fasting.

Intravenous access is not thought to be necessary for all pediatric patients sedated for a diagnostic or therapeutic procedure because in some cases the difficulty of gaining IV access would defeat the purpose of sedating the child; rather, emphasis should be placed upon having the intravenous equipment available and a practitioner skilled in establishing vascular access in pediatric patients immediately available.

Midazolam HCl syrup must never be used without individualization of dosage, particularly when used with other medications capable of producing CNS depression. Younger (<6 years of age) pediatric patients may require higher dosages (mg/kg) than older pediatric patients, and may require close monitoring.

When midazolam HCl syrup is given in conjunction with opioids or other sedatives, the potential for respiratory depression, airway obstruction, or hypoventilation is increased. For appropriate patient monitoring, see and subsection of . The health care practitioner who uses this medication in pediatric patients should be aware of and follow accepted professional guidelines for pediatric sedation appropriate to their situation. WARNINGSMonitoring DOSAGE AND ADMINISTRATION

The recommended dose for pediatric patients is a single dose of 0.25 to 0.5 mg/kg, depending on the status of the patient and desired effect, up to a maximum dose of 20 mg. In general, it is recommended that the dose be individualized and modified based on patient age, level of anxiety, concomitant medications, and medical need (see and). The younger (6 months to <6 years of age) and less cooperative patients may require a higher than usual dose up to 1.0 mg/kg. A dose of 0.25 mg/kg may suffice for older (6 to <16 years of age) or cooperative patients, especially if the anticipated intensity and duration of sedation is less critical. For all pediatric patients, a dose of 0.25 mg/kg should be considered when midazolam HCl syrup is administered to patients with cardiac or respiratory compromise, other higher risk surgical patients, and patients who have received concomitant narcotics or other CNS depressants. As with any potential respiratory depressant, these patients must be monitored for signs of cardiorespiratory depression after receiving midazolam HCl syrup. In obese pediatric patients, the dose should be calculated based on ideal body weight. Midazolam HCl syrup has not been studied, nor is it intended for chronic use. WARNINGSPRECAUTIONS

INSERTION OF PRESS-IN BOTTLE ADAPTER (PIBA)

1.Remove the cap and push bottle

adapter into neck of bottle.

2.Close the bottle tightly with cap.

This will assure the proper seating of

the bottle adapter in the bottle

USE OF ORAL DISPENSERS AND PIBA

1.Remove the cap.

2.Before inserting the tip of the oral

dispenser into bottle adapter, push

the plunger completely down toward

the tip of the oral dispenser. Insert

tip firmly into opening of the bottle

adapter.

3.Turn the entire unit (bottle and oral

dispenser) upside down.

4.Pull the plunger out slowly until the

desired amount of medication is

withdrawn into the oral dispenser.

5.Turn the entire unit right side up and

remove the oral dispenser slowly from

the bottle.

6.The tip of the dispenser may be covered with a tip cap, until time of use.

7.Close bottle with cap after each use.

8.Dispense directly into mouth. Do not mix with any liquid (such as grapefruit juice) prior to dispensing.

DISPOSAL OF MIDAZOLAM HCl SYRUP

The disposal of Schedule IV controlled substances must be consistent with State and Federal Regulations

HOW SUPPLIED

NDC:17856-3566-1 in a CUP of 2 SYRUPS

NDC:17856-3566-3 in a CUP of 5 SYRUPS